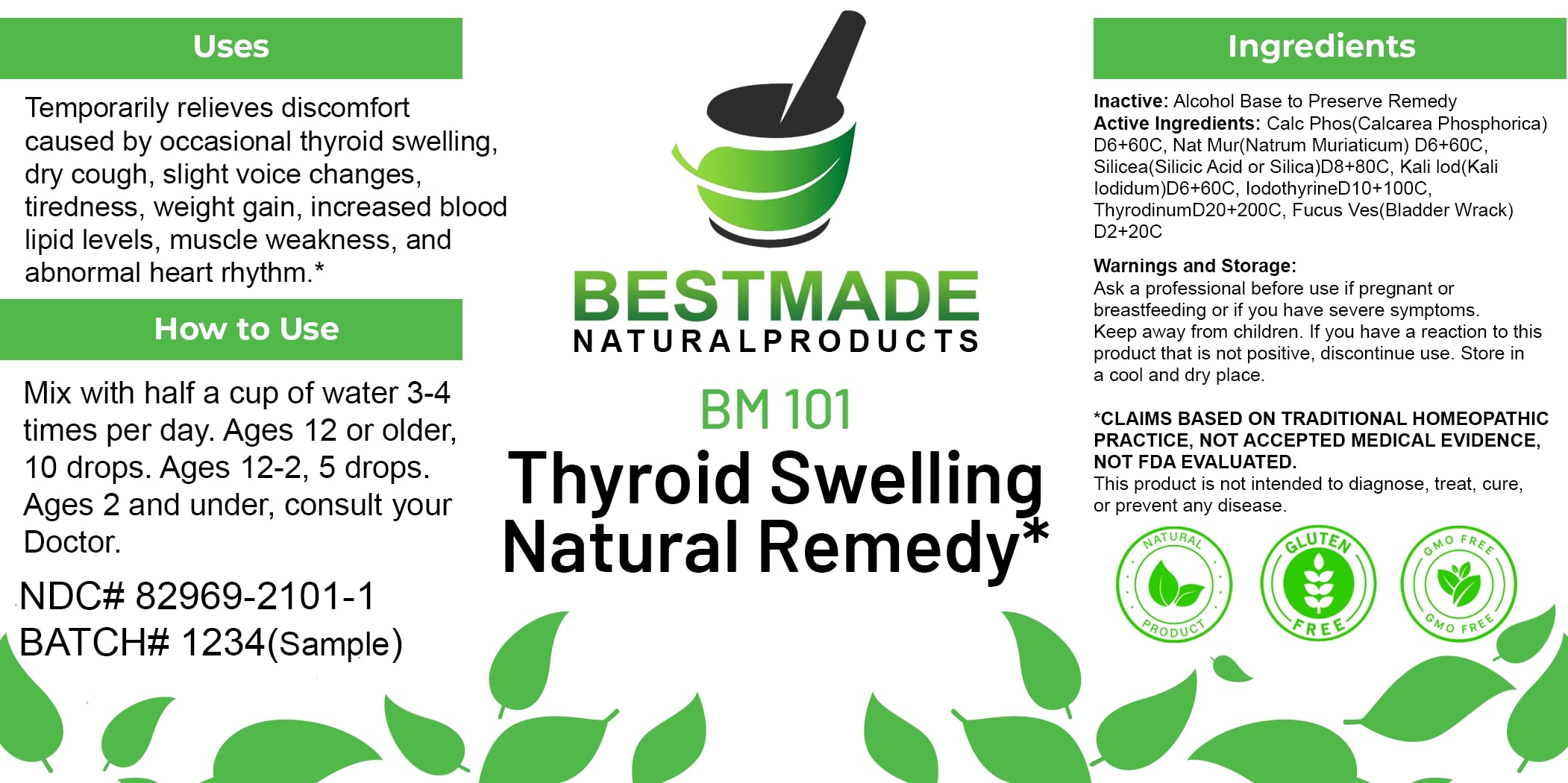 DRUG LABEL: Bestmade Natural Products BM101
NDC: 82969-2101 | Form: LIQUID
Manufacturer: Bestmade Natural Products
Category: homeopathic | Type: HUMAN OTC DRUG LABEL
Date: 20250206

ACTIVE INGREDIENTS: FUCUS VESICULOSUS 30 [hp_C]/30 [hp_C]; TRIBASIC CALCIUM PHOSPHATE 30 [hp_C]/30 [hp_C]; SODIUM CHLORIDE 30 [hp_C]/30 [hp_C]; THYROID, UNSPECIFIED 30 [hp_C]/30 [hp_C]; SILICA 30 [hp_C]/30 [hp_C]; POTASSIUM IODIDE 30 [hp_C]/30 [hp_C]
INACTIVE INGREDIENTS: ALCOHOL 30 [hp_C]/30 [hp_C]

BM101

DOSAGE AND ADMINISTRATION

How to Use

Mix with half a cup of water 3-4 times per day. Ages 12 or older, 10 drops. Ages 12-2, 5 drops. Ages 2 and under, consult your Doctor.

INACTIVE INGREDIENT

Ingredients

Inactive: Alcohol Base to Preserve Remedy

ACTIVE INGREDIENT

Active Ingredients: Calc Phos (Calcarea Phosphonica) D6+60C, Nat Mur (Natrum Muriaticum) D6+60C, Silicea (Silicic Acid or Silica) D6+60C, Kali Iod (Kali Iodidum) D6+60C, Iodothyrid 10+100C, Thyrodinum D20+200C, Fucus Ves (Bladder Wrack) D2+20C

Uses

Temporarily relieves discomfort caused by occasional thyroid swelling, dry cough, slight voice changes, tiredness, weight gain, increased blood lipid levels, muscle weakness, and abnormal heart rhythm.*

*CLAIMS BASED ON TRADITIONAL HOMEOPATHIC PRACTICE, NOT ACCEPTED MEDICAL EVIDENCE, NOT FDA EVALUATED.

This product is not intended to diagnose, treat, cure, or prevent any disease.

KEEP OUT OF REACH OF CHILDREN

Warnings and Storage:

Ask a professional before use if pregnant or breastfeeding or if you have severe symptoms. Keep away from children. If you have a reaction to this product that is not positive, discontinue use. Store in a cool and dry place.

Uses

Temporarily relieves discomfort caused by occasional thyroid swelling, dry cough, slight voice changes, tiredness, weight gain, increased blood lipid levels, muscle weakness, and abnormal heart rhythm.*

*CLAIMS BASED ON TRADITIONAL HOMEOPATHIC PRACTICE, NOT ACCEPTED MEDICAL EVIDENCE, NOT FDA EVALUATED.

This product is not intended to diagnose, treat, cure, or prevent any disease.

Warnings and Storage:

Ask a professional before use if pregnant or breastfeeding or if you have severe symptoms. Keep away from children. If you have a reaction to this product that is not positive, discontinue use. Store in a cool and dry place.

*CLAIMS BASED ON TRADITIONAL HOMEOPATHIC PRACTICE, NOT ACCEPTED MEDICAL EVIDENCE, NOT FDA EVALUATED.

This product is not intended to diagnose, treat, cure, or prevent any disease.

Entire package label